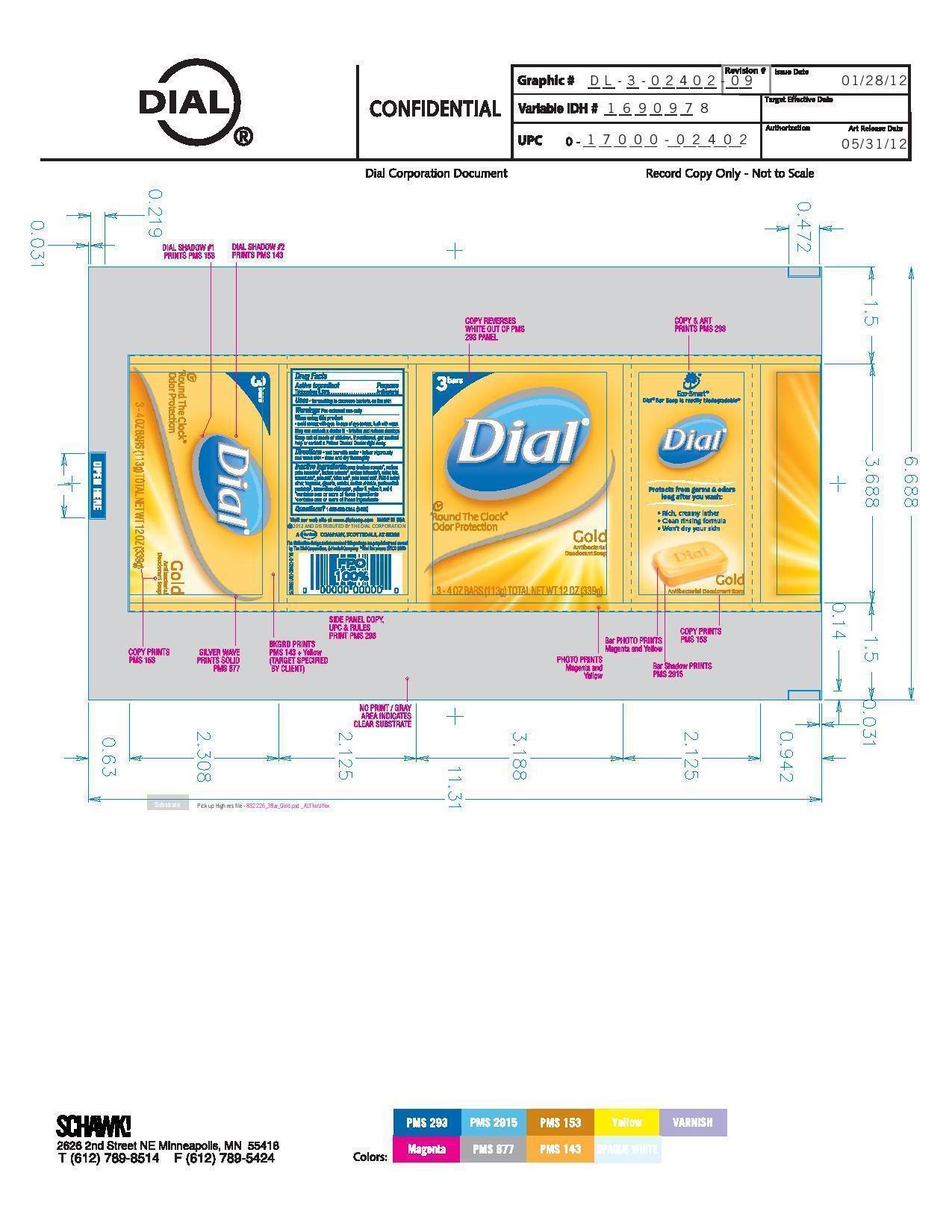 DRUG LABEL: Dial antibacterial
NDC: 51815-300 | Form: SOAP
Manufacturer: VVF Illinois Services LLC
Category: otc | Type: HUMAN OTC DRUG LABEL
Date: 20130529

ACTIVE INGREDIENTS: TRICLOCARBAN .339 g/113 g
INACTIVE INGREDIENTS: SODIUM COCOATE; SODIUM PALM KERNELATE; SODIUM PALMATE; SODIUM TALLOWATE, BEEF; WATER; TALC; COCONUT ACID; PALM ACID; TALLOW ACID, BEEF; PALM KERNEL ACID; PEG-6 METHYL ETHER; GLYCERIN; SORBITOL; SODIUM CHLORIDE; PENTASODIUM PENTETATE; ETIDRONATE TETRASODIUM; FD&C YELLOW NO. 5; D&C YELLOW NO. 8; FD&C RED NO. 4

Dial Gold

Active ingredient

Triclocarban 0.30%

Purpose

Antibacterial

Keep out of reach of children.

If swallowed, get medical

help or contact Poison Control right away.

Use

For washing to decrease bacteria on the skin

Warnings

For external use only

When using this product

- Avoid contact with eyes. In case of eye contact, flush with water

Stop using and ask doctor if irritation and redness develops

Directions

wet bar with water - lather vigorously -

and wash skin - rinse and dry thoroughly

Inactive ingredients

soap (sodium cocoate*, sodium

palm kernelate*, sodium palmate*, sodium tallowate*), water, talc

coconut acid*, palm acid*, tallow acid*, palm kernel acid*, PEG-6 methyl

ether, fragrance, glycerin, sorbitol, sodium chloride, pentasodium

pentate^1, tetra sodium etidronate^1, yellow 5, yellow 8, red 4

*contains one or more of these ingredients

^1contains one or more of these ingredients